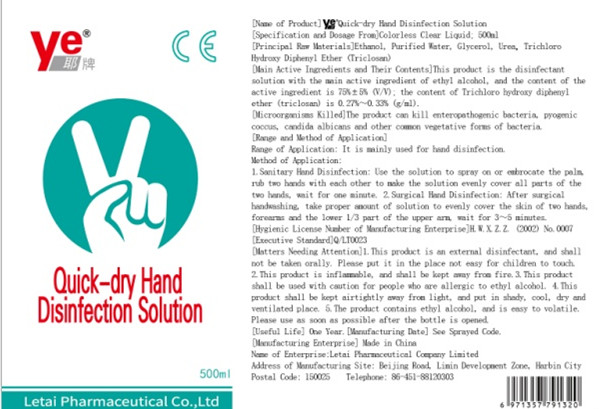 DRUG LABEL: yeQuick-dry Hand Disinfection Solution
NDC: 52716-001 | Form: GEL
Manufacturer: Letai Pharmaceutical Co., Ltd.
Category: otc | Type: HUMAN OTC DRUG LABEL
Date: 20200413

ACTIVE INGREDIENTS: ALCOHOL 375 mL/500 mL
INACTIVE INGREDIENTS: GLYCERIN; UREA; WATER

DOSAGE AND ADMINISTRATION

Proper amount

INACTIVE INGREDIENT

Glycerine

Urea

Purified water

ACTIVE INGREDIENT

alcohol

keep out of reach of cildren section

PURPOSE

Make hands clean quickly

INDICATIONS AND USAGE

1. Hygienic hand disinfection: Mist or rub the original liquid evenly on the palm of the hand. Rub your hands together to evenly coat each part for 1 minute.

2.Surgical hand disinfection: After washing hands, take appropriate amount of the original liquid and apply it to the skin of the hands, forearm and upper 1/3 of the lower arm. Act for 3 ~ 5 minutes.

WARNINGS

1. This product is a disinfectant for external use and should not be taken orally. Keep out of the reach of children.
2. This product is flammable and should be kept away from fire.
3. For those who are allergic to ethanol.
4. Keep in air, keep away from light and store in a cool, dry and ventilated place.
5. This product contains ethanol and is volatile. Please use as soon as possible after opening the bottle.